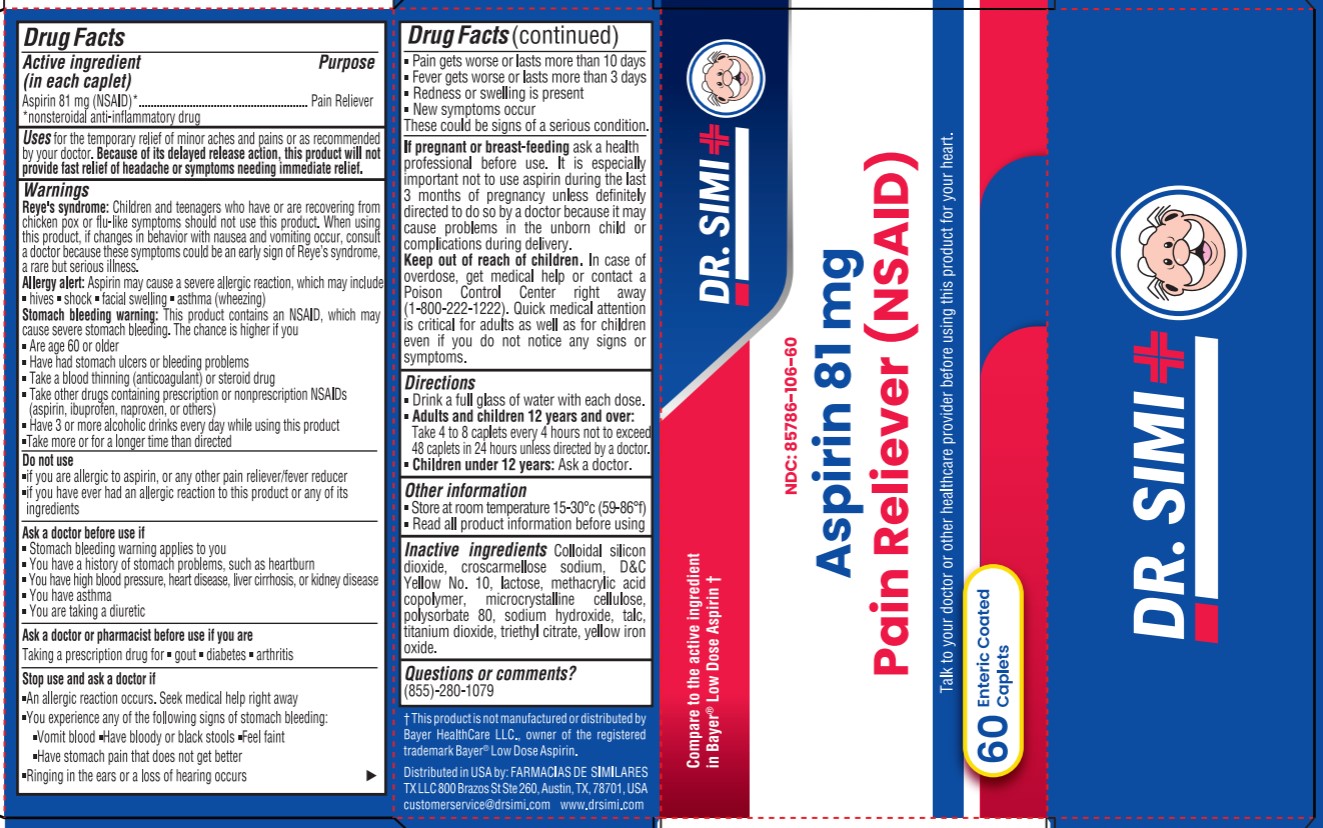 DRUG LABEL: ASPIRIN DELAYED RELEASE 81MG
NDC: 85786-106 | Form: TABLET, COATED
Manufacturer: Farmacias De Similares TX LLC
Category: otc | Type: HUMAN OTC DRUG LABEL
Date: 20260113

ACTIVE INGREDIENTS: ASPIRIN 81 mg/1 1
INACTIVE INGREDIENTS: BUTYL ACRYLATE/METHYL METHACRYLATE/METHACRYLIC ACID COPOLYMER (18000 MW); LACTOSE; TALC; POLYSORBATE 80; D&C YELLOW NO. 10; MICROCRYSTALLINE CELLULOSE; SODIUM HYDROXIDE; TITANIUM DIOXIDE; TRIETHYL CITRATE; SILICON DIOXIDE; CROSCARMELLOSE SODIUM; FERRIC OXIDE YELLOW

Active ingredient (in each caplet)

Aspirin 81 mg (NSAID)*
*nonsteroidal anti-inflammatory drug

Purpose

Pain Reliever

Uses

for the temporary relief of minor aches and pains or as recommended by your doctor. Because of its delayed release action, this product will not provide fast relief of headache or symptoms needing immediate relief.

Warnings

Reye's syndrome: Children and teenagers who have or are recovering from chicken pox or flu-like symptoms should not use this product. When using this product, if changes in behavior with nausea and vomiting occur, consult a doctor because these symptoms could be an early sign of Reye's syndrome, a rare but serious illness.

Allergy alert: Aspirin may cause a severe allergic reaction, which may include
. hives . shock . facial swelling . asthma (wheezing)

Stomach bleeding warning: This product contains an NSAID, which may cause severe stomach bleeding. The chance is higher if you
. Are age 60 or older
. Have had stomach ulcers or bleeding problems
. Take a blood thinning (anticoagulant) or steroid drug
. Take other drugs containing prescription or nonprescription NSAIDs (aspirin, ibuprofen, naproxen, or others)
. Have 3 or more alcoholic drinks every day while using this product.
. Take more or for a longer time than directed

Do not use

. if you are allergic to aspirin, or any other pain reliever/fever reducer
. if you have ever had an allergic reaction to this product or any of its ingredients

Ask a doctor before use if

. Stomach bleeding warning applies to you
. You have a history of stomach problems, such as heartburn
. You have high blood pressure, heart disease, liver cirrhosis, or kidney disease
. You have asthma
. You are taking a diuretic

Ask a doctor or pharmacist before use if you are

Taking a prescription drug for . gout . diabetes . arthritis

Stop use and ask a doctor if

. An allergic reaction occurs. Seek medical help right away

. You experience any of the following signs of stomach bleeding:
-Vomit blood -Have bloody or black stools -Feel faint -Have stomach pain that does not get better

. Ringing in the ears or a loss of hearing occurs

. Pain gets worse or lasts more than 10 days

. Fever gets worse or lasts more than 3 days

. Redness or swelling is present

. New symptoms occur

These could be signs of a serious condition.

If pregnant or breast-feeding

ask a health professional before use. It is especially important not to use aspirin during the last 3 months of pregnancy unless definitely directed to do so by a doctor because it may cause problems in the unborn child or complications during delivery.

Keep out of reach of children.

In case of overdose

get medical help or contact a Poison Control Center right away (1-800-222-1222). Quick medical attention is critical for adults as well as for children even if you do not notice any signs or symptoms.

Directions

. Drink a full glass of water with each dose.
. Adults and children 12 years and over:
Take 4 to 8 caplets every 4 hours not to exceed 48 caplets in 24 hours unless directed by a doctor.
. Children under 12 years: Ask a doctor.

Other information

. Store at room temperature 15-30°C (59-86°F)
. Read all product information before using

Inactive ingredients

Colloidal silicon dioxide, croscarmellose sodium, D&C Yellow No. 10, lactose, methacrylic acid copolymer, microcrystalline cellulose, polysorbate 80, sodium hydroxide, talc, titanium dioxide, triethyl citrate, yellow iron oxide

Questions or comments?

(855)-280-1079

t This product is not manufactured or distributed by Bayer HealthCare LLC., owner of the registered trademark Bayer® Low Dose Aspirin.

Distributed in USA by: FARMACIAS DE SIMILARES
TXLLC 800 Brazos St Ste 260, Austin, TX, 78701, USA
customerservice@drsimi.com www.drsimi.com

PACKAGE LABEL

Dr. Simi

Compare to the active ingredient in Bayer® Low Dose Aspirin t

NDC: 85786-106-60

Aspirin 81 mg
Pain Reliever (NSAID)

Talk to your doctor or other healthcare provider before using this product for your heart.

60 Enteric Coated Caplets